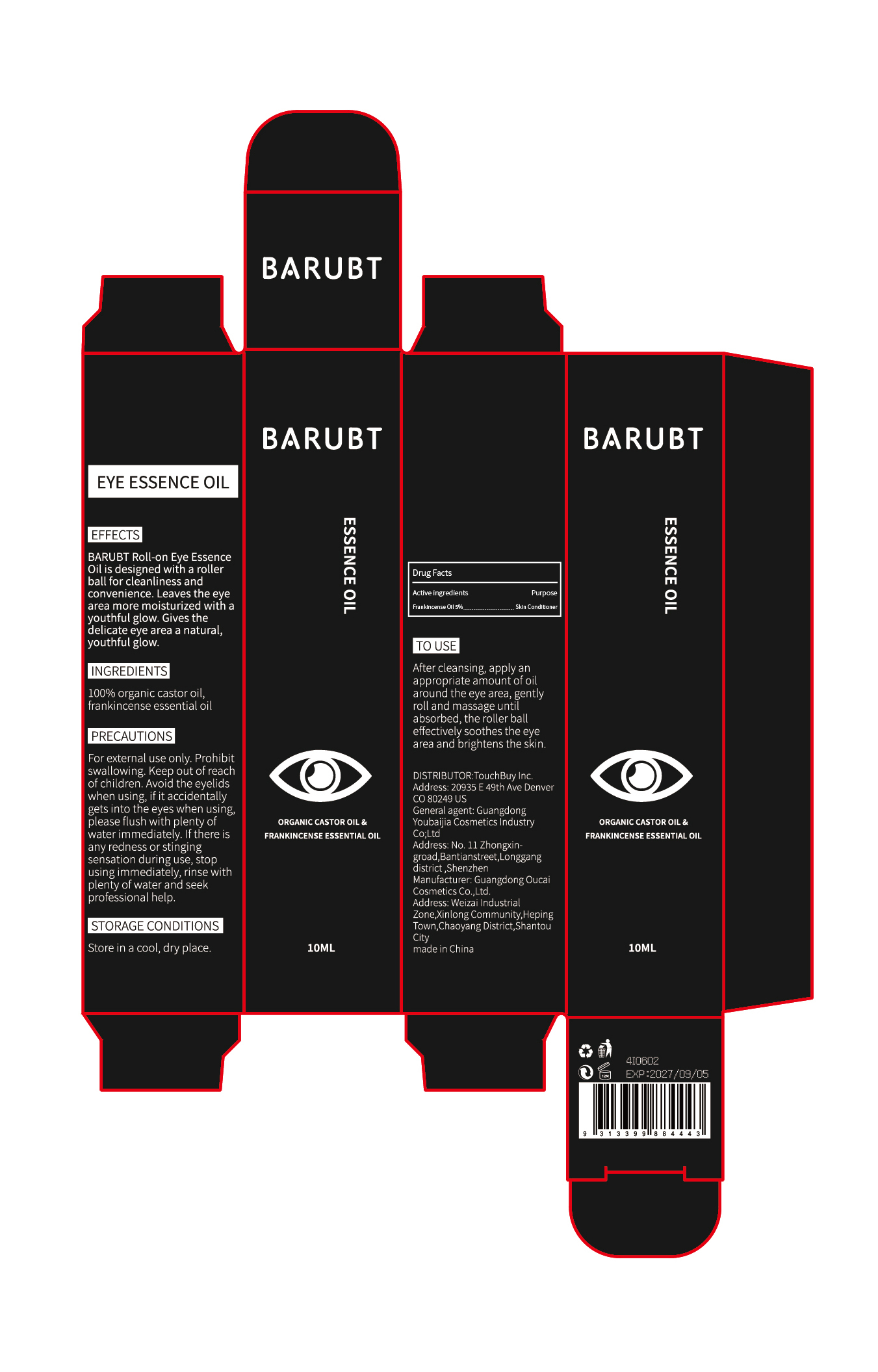 DRUG LABEL: BARUBT Eye Essence Oil
NDC: 84712-032 | Form: OIL
Manufacturer: Guangdong Youbaijia Cosmetic Industry Co., Ltd
Category: otc | Type: HUMAN OTC DRUG LABEL
Date: 20241028

ACTIVE INGREDIENTS: FRANKINCENSE OIL 0.5 g/10 mL
INACTIVE INGREDIENTS: CASTOR OIL 9.5 g/10 mL

ACTIVE INGREDIENT

frankincense essential oil 5%

INACTIVE INGREDIENT

100% organic castor oil

INDICATIONS AND USAGE

EFFECTS
BARUBT Roll-on Eye Essence Oil is designed with a roller ball for cleanliness and convenience. Leaves the eye area more moisturized with a youthful glow. Gives the delicate eye area a natural,youthful glow.

Do not use on damaged or broken skin

Prohibit swallowing. Keep out of reach of children

PURPOSE

moisturized with a youthful glow

QUESTIONS

Contact name: Jessie Peng
Company phone number: +1 818 579 7288
Company e-mail: jessie@registeragentllc.com

STOP USE

lf there is any redness or stinging sensation during use, stop using immediately, rinse with plenty of water and seek professional help.

WHEN USING

Avoid the eyelids when using, if it accidentally gets into the eyes when using,please flush with plenty of water immediately.

WARNINGS

For external use only.

STORAGE AND HANDLING

Storage conditions:Keep away from light and in a dry place.

DOSAGE AND ADMINISTRATION

After cleansing, apply an appropriate amount of oil around the eye area, gently roll and massage until absorbed, the roller ball effectively soothes the eye area and brightens the skin.